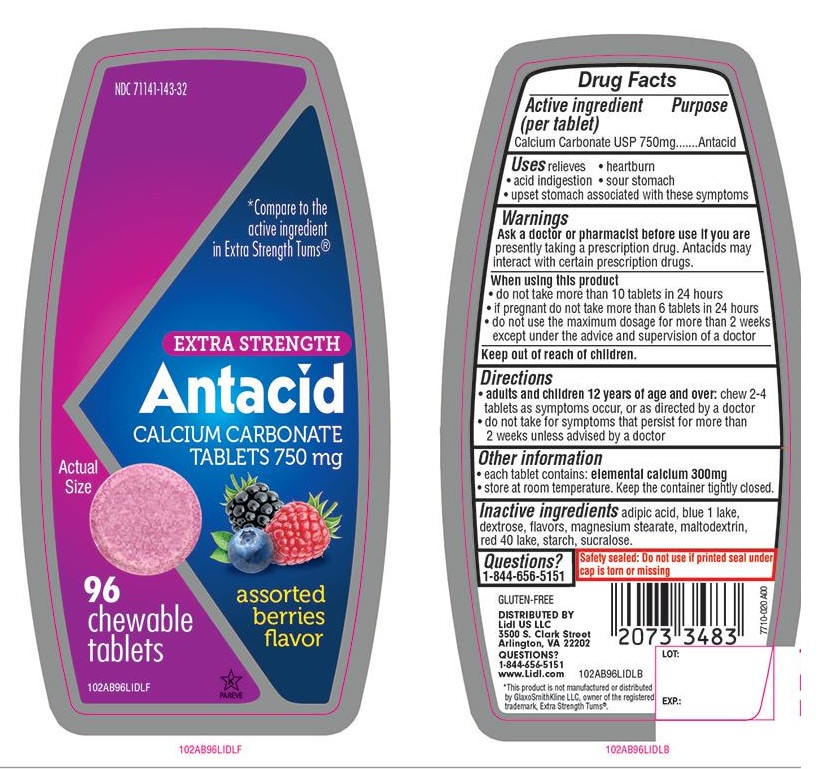 DRUG LABEL: Extra Strength Antacid

NDC: 71141-143 | Form: TABLET, CHEWABLE
Manufacturer: LIDL US, LLC
Category: otc | Type: HUMAN OTC DRUG LABEL
Date: 20250919

ACTIVE INGREDIENTS: CALCIUM CARBONATE 750 mg/1 1
INACTIVE INGREDIENTS: ADIPIC ACID; FD&C BLUE NO. 1; DEXTROSE, UNSPECIFIED FORM; MAGNESIUM STEARATE; MALTODEXTRIN; FD&C RED NO. 40; STARCH, CORN; SUCRALOSE

LIDL Extra Strength Antacid Calcium Carbonate Assorted Berries Chewable Tablets

Active ingredient (per tablet)

Calcium Carbonate USP 750mg

Purpose

Antacid

Uses

relieves

- heartburn
- acid indigestion
- sour stomach
- upset stomach associated with these symptoms

Warnings

Ask a doctor or pharmacist before use if you arepresently taking a prescription drug. Antacids may interact with certain prescription drugs.

When using this product

- do not take more than 10 tablets in 24 hours
- If pregnant do not take more than 6 tablets in 24 hours
- do not use the maximum dosage for more than 2 weeks except under the advice and supervision of a doctor

Directions

- adults and children 12 years of age and over:chew 2-4 tablets as symptoms occur, or as directed by a doctor
- do not take for symptoms that persist for more than 2 weeks unless advised by a doctor

Other Information

- each tablet contains: elemental calcium 300mg
- store at room temperature. Keep the container tightly closed.

Inactive ingredients

adipic acid, blue 1 lake, dextrose, flavors, magnesium stearate, maltodextrin, red 40 lake, starch, sucralose.

Questions?

1-844-656-5151

Safety sealed: Do not use if printed seal under cap is torn or missing

Package/Label Principal Display Panel

NDC 71141-143-32

*Compare to the active ingredient in Extra Strength Tums®

EXTRA STRENGTH

Antacid

CALCIUM CARBONATE TABLETS 750 mg

assorted berries flavor

96 chewable tablets

GLUTEN-FREE

DISTRIBUTED BY

Lidl US LLC

3500 S. Clark Street

Arlington, VA 22202

QUESTIONS?

1-844-656-5151

www.Lidl.com

*This product is not manufactured or distributed by GlaxoSmithKline LLC, owner of the registered trademark, Extra Strength Tums®.